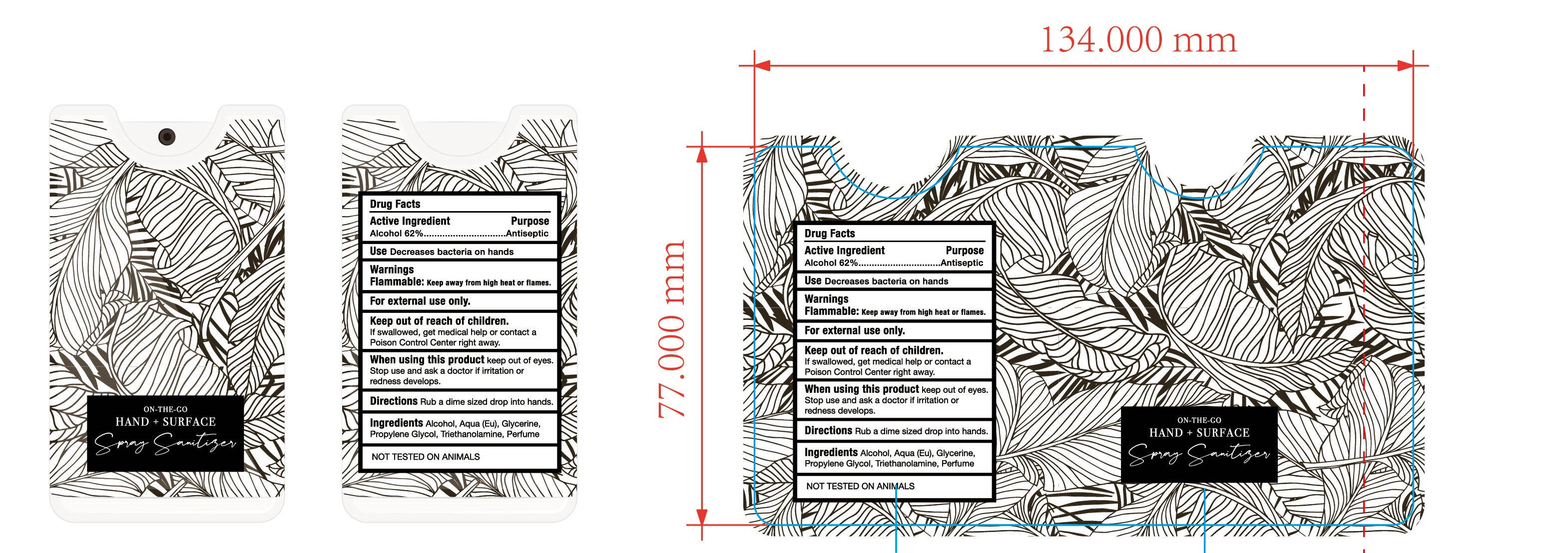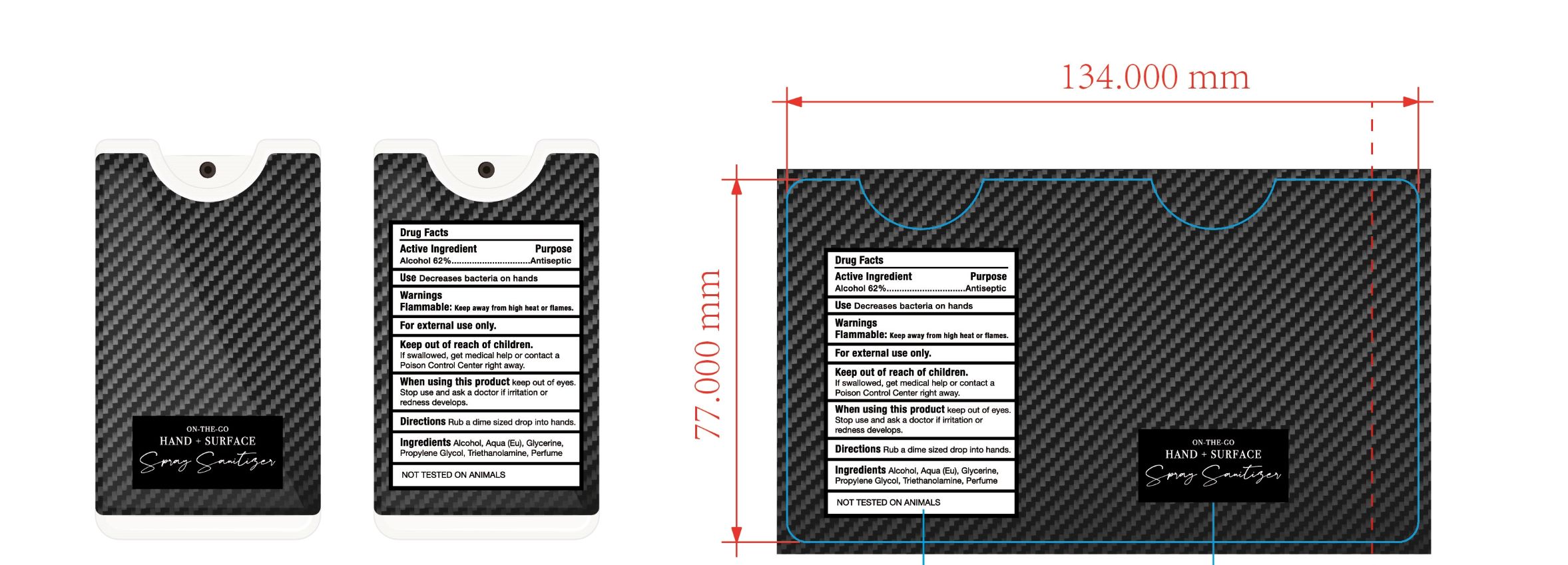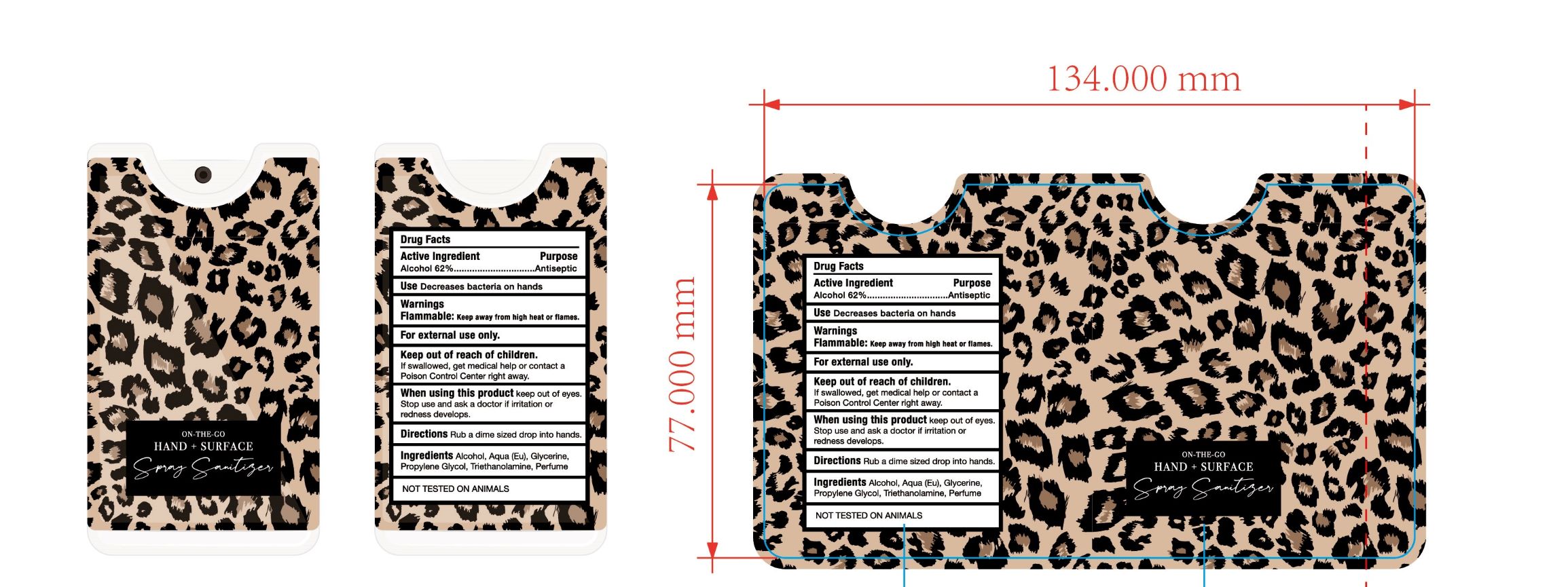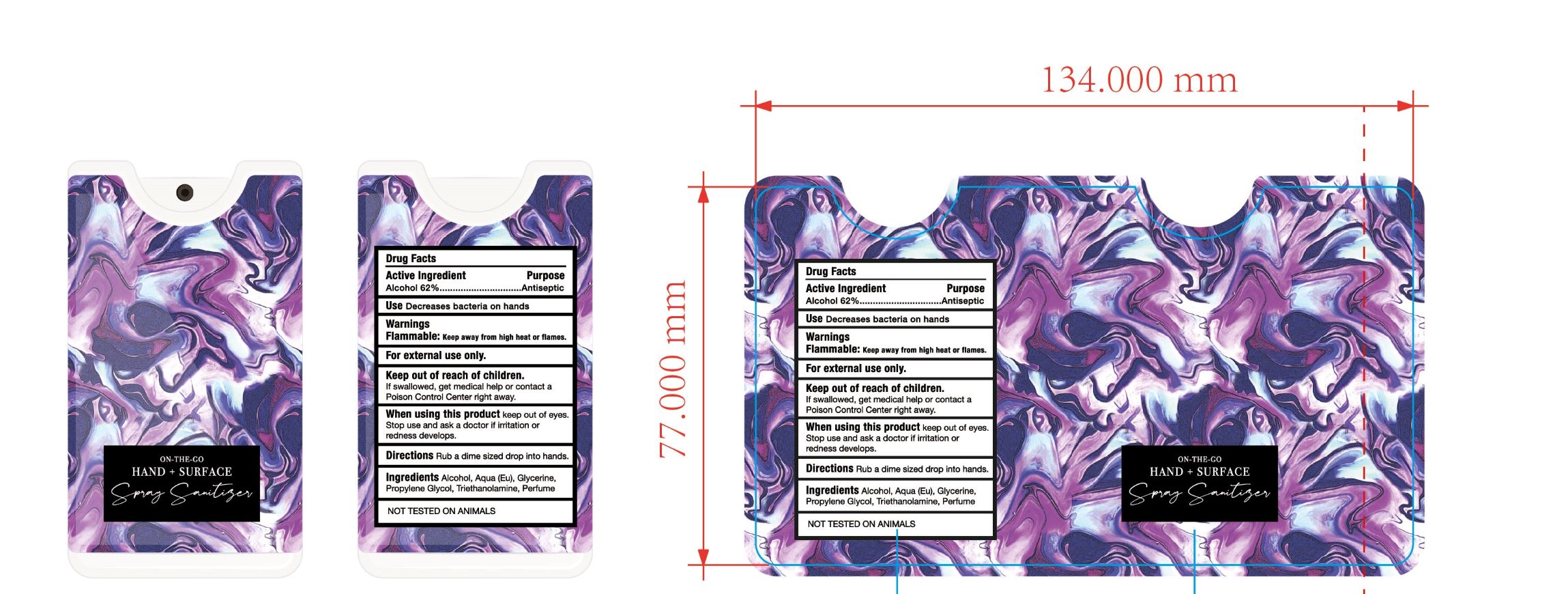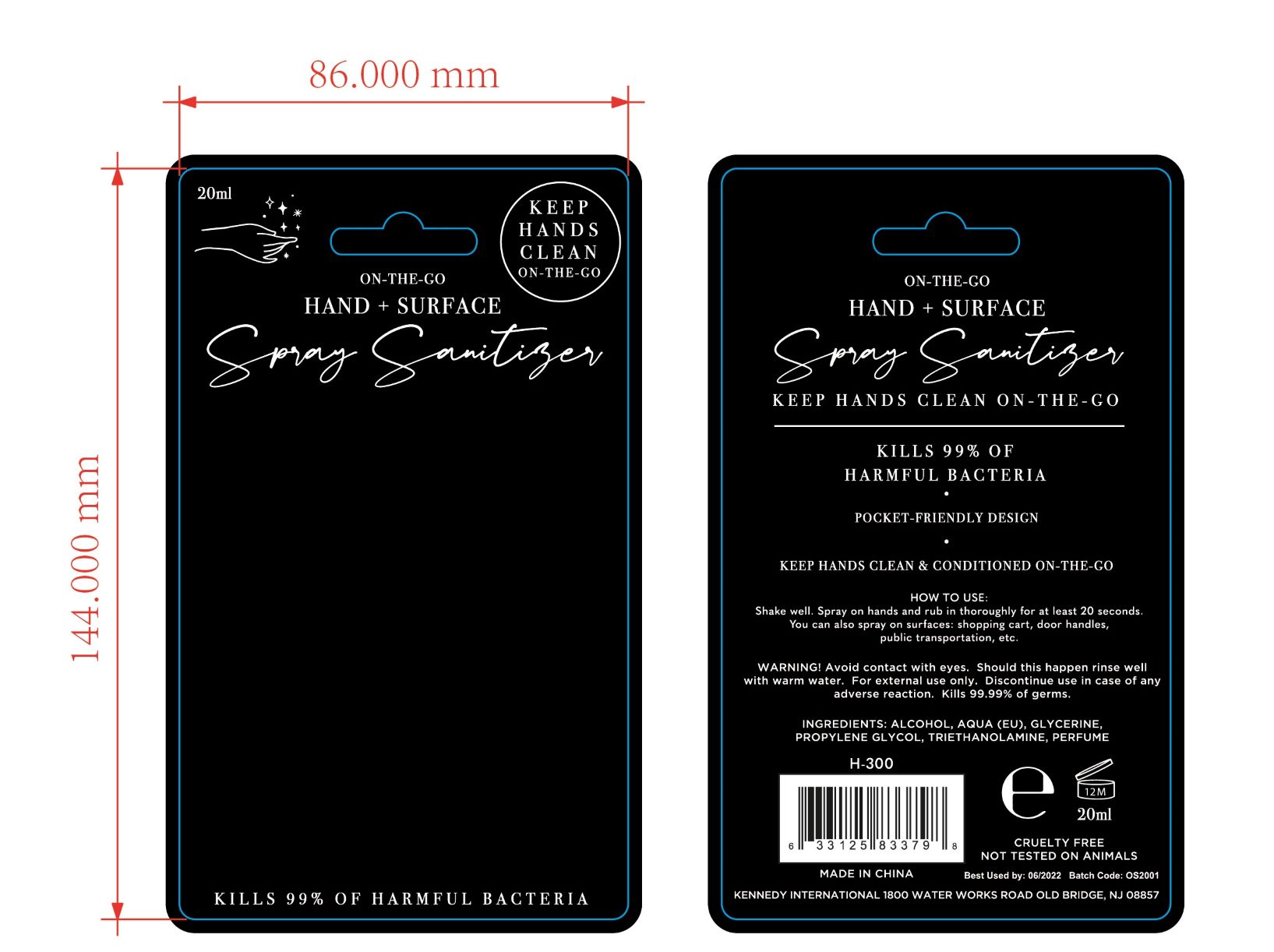 DRUG LABEL: HAND SURFACE SPRAYSANITIZER
NDC: 47993-311 | Form: LIQUID
Manufacturer: NINGBO JIANGBEI OCEAN STAR TRADING CO.,LTD
Category: otc | Type: HUMAN OTC DRUG LABEL
Date: 20201105

ACTIVE INGREDIENTS: ALCOHOL 62 g/112 mL
INACTIVE INGREDIENTS: WATER; GLYCERIN; PROPYLENE GLYCOL; TRIETHANOLAMINE BENZOATE

47993-311

Active ingredients

Alcohol 62%

PURPOSE

Antiseptic

Uses：

Decreases bacteria on hands.

Warnings:

Flammable: Keep away from high heat or flames.

For external use only.

Keep out of reach of children.

If swallowed, get medical help or contact a Poison Control Center right away.

When using this product keep out of eyes.

Stop use and ask a doctor if irritation or redness develops.

Directions:

Rub a dime sized drop into hands.

Inactive Ingredients:

Aqua(Eu),Glycerine,Propylene Glycol,Triethanolamine,Perfume